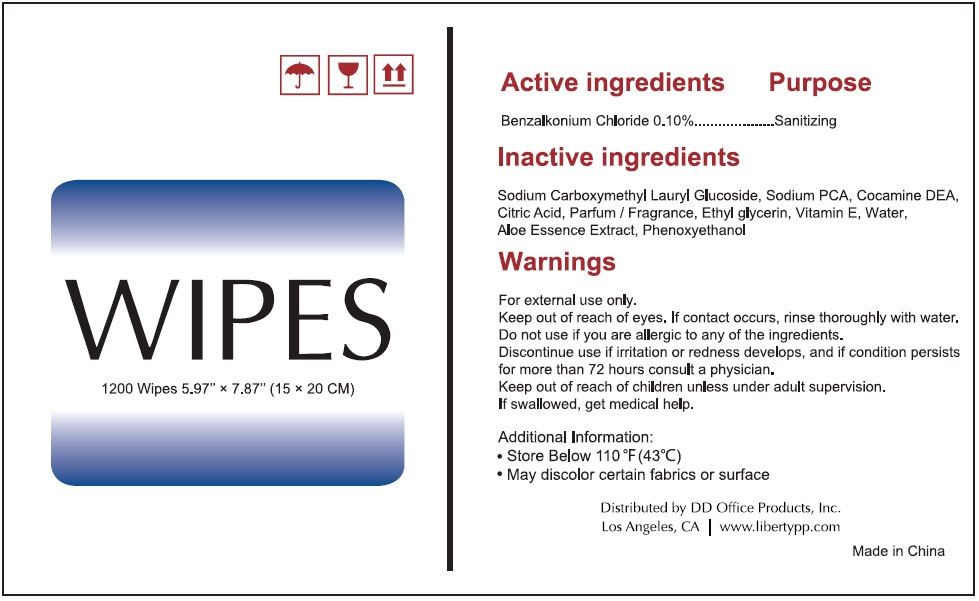 DRUG LABEL: 1200 Wet Wipes
NDC: 77081-001 | Form: CLOTH
Manufacturer: D D Office Products, Inc.
Category: otc | Type: HUMAN OTC DRUG LABEL
Date: 20200713

ACTIVE INGREDIENTS: BENZALKONIUM CHLORIDE 0.1 g/100 mL
INACTIVE INGREDIENTS: CARBOXYMETHYLCELLULOSE SODIUM, UNSPECIFIED; LAURYL GLUCOSIDE; SODIUM PYRROLIDONE CARBOXYLATE; COCO DIETHANOLAMIDE; CITRIC ACID MONOHYDRATE; ETHYLHEXYLGLYCERIN; .ALPHA.-TOCOPHEROL; WATER; ALOE VERA LEAF; PHENOXYETHANOL

1200 WIPES

Active ingredients

Benzalkonium Chloride 0.10%

Purpose

Sanitizing

Use

hand sanitizer to decrease bacteria on the skin.

Warnings

For external use only.

Keep out of reach of eyes. If contact occurs, rinse thoroughly with water.

Do not use if you are allergic to any of the ingredients.

Discontinue use if irritation or redness develops, and if condition persists for more than 72 hours consult a physician.

Keep out of reach of children unless under adult supervision.

If swallowed, get medical help

DOSAGE AND ADMINISTRATION

Direction

Wet hands thoroughly with product and allow to dry without wiping.

Additional Information:

• Store below 110°F (43°C).

• May discolor certain fabrics or surfaces.

Inactive ingredients

Sodium Carboxymethyl Lauryl Glucoside, Sodium PCA, Cocamide DEA, Citric Acid, Parfum / Fragrance, Ethyl glycerin, Vitamin E, Water, Aloe Essence Extract, Phenoxyethanol

Distributed by DD Office Products, Inc.

Los Angeles, CA | www.libertypp.com

Made in China